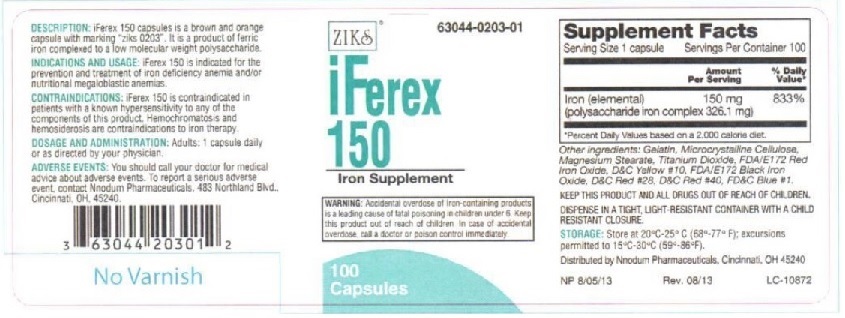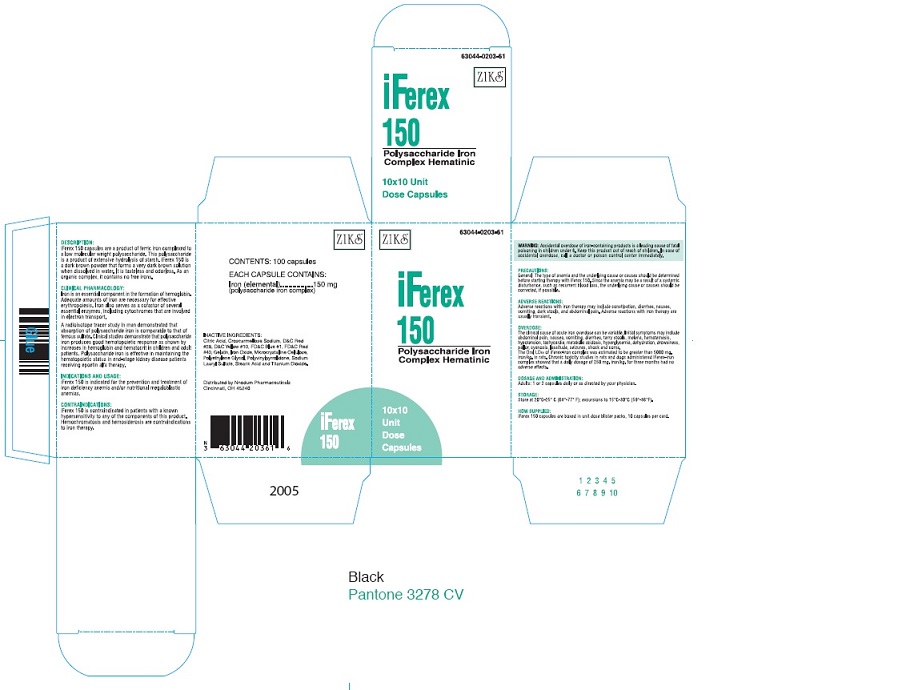 DRUG LABEL: IFEREX 150
NDC: 63044-203 | Form: CAPSULE
Manufacturer: Nnodum Pharmaceuticals
Category: other | Type: Dietary Supplement
Date: 20251229

ACTIVE INGREDIENTS: IRON 150 mg/1 1
INACTIVE INGREDIENTS: FERROSOFERRIC OXIDE; FD&C BLUE NO. 1; FD&C RED NO. 40; FD&C YELLOW NO. 6; GELATIN; MAGNESIUM STEARATE; CELLULOSE, MICROCRYSTALLINE; FERRIC OXIDE RED; TITANIUM DIOXIDE

iFEREX 150

Statement of identity

iFEREX 150 is an easily assimilated source of iron for treatment of uncomplicated iron deficiency anemia.

Healthn Claims

iFerex 150 is indicated for the prevention and treatment of iron deficiency anemia and/or nutritional megaloblastic anemias.

Warning

Accidental overdose of iron-containing products is a leading cause in fatal poisoning of children under 6. Keep this product out of reach of children. In case of accidental overdose, call a doctor or poison control center immediately.

Dosage and Administration

Adults: One or two capsules daily or as directed by a physician.

Precautions

General: The type of anemia and underlying cause or causes should be determined before starting therapy with iFerex 150. Since the

anemia may be a result of systemic disturbance, such as recurrent blood loss, the underlying cause or causes should be corrected, if possible.

Safe Handling Warning

KEEP THIS AND ALL DRUGS OUT OF REACH OF CHILDREN.

DISPENSE IN A TIGHT, LIGHT-RESISTANT CONTAINER WITH A RESISTANT CLOSURE.

STORAGE: Store at 20oC-25oC (68o- 77oF); excursions to 15oC-30oC (59o-86oF)

Principal Display Panel - IFEREX 150

ZIKs 63044-0203-01

iFEREX 150

Polysaccharide Iron

Complex Hematinic

100 Capsules

EACH CAPSULE CONTAINS:

Iron (elemental).....................150 mg

(polysaccharide iron complex 326.1 mg)

INACTIVE INGREDIENTS: Black Iron oxide,FD&C Red #28, FD&C Yellow # 10, FD&C blue #1, FD&C red #40, FD&C yellow #6,gelatin, magnesium stearate, microcrystalline cellulose,Red Iron Oxide, and Titanium Dioxide

DESCRIPTION: iFerex 150 is a brown and orange capsule with marking "ziks 0203".

It is a product of ferric iron complexed to a low molecular weight polysaccharide.

INDICATIONS AND USAGE: iFerex 150 is indicated for the prevention and treatment of

iron deficiency anemia and/or nutritional megaloblastic anemias.

CONTRAINDICATIONS: iFerex 150 is indicated in patients with a known hypersensitivity

to any of the components of this product. Hemochromatosis and hemosiderosis are

contraindications to iron therapy.

ADVERSE REACTIONS: Adverse reactions with iron therapy may include constipation,

diarrhea, nausea, vomiting, dark stools, and abdomibal pain. Adverse reactions with iron

tharapy are usually transient.

WARNING: Accidental overdose of iron-containing products is a leading cause in

fatal poisoning of children under 6. Keep this product out of reach of children.

In case of accidental overdose, call a doctor or poison control center immediately.

PRECAUTIONS: General: The type of anemia and underlying cause or causes

should be determined before starting therapy with iFerex 150. Since the

anemia may be a result of systemic disturbance, such as recurrent blood loss,

the underlying cause or causes should be corrected, if possible.

DOSAGE AND ADMINISTRATION: Adults: One or two capsules daily or as directed by a physician.

KEEP THIS AND ALL DRUGS OUT OF REACH OF CHILDREN.

DISPENSE IN A TIGHT, LIGHT-RESISTANT CONTAINER WITH A RESISTANT CLOSURE.

STORAGE: Store at 20oC-25oC (68o- 77oF); excursions to 15oC-30oC (59o-86oF)

HOW SUPPLIED: iFerex 150 capsules are supplied in 100 capsule per bottle.

Distributed by Nnodum Pharmaceuticals, Cincinnati, OH 45229

NP 6/18/09

LC-10872

3 63044 20301 2

reg